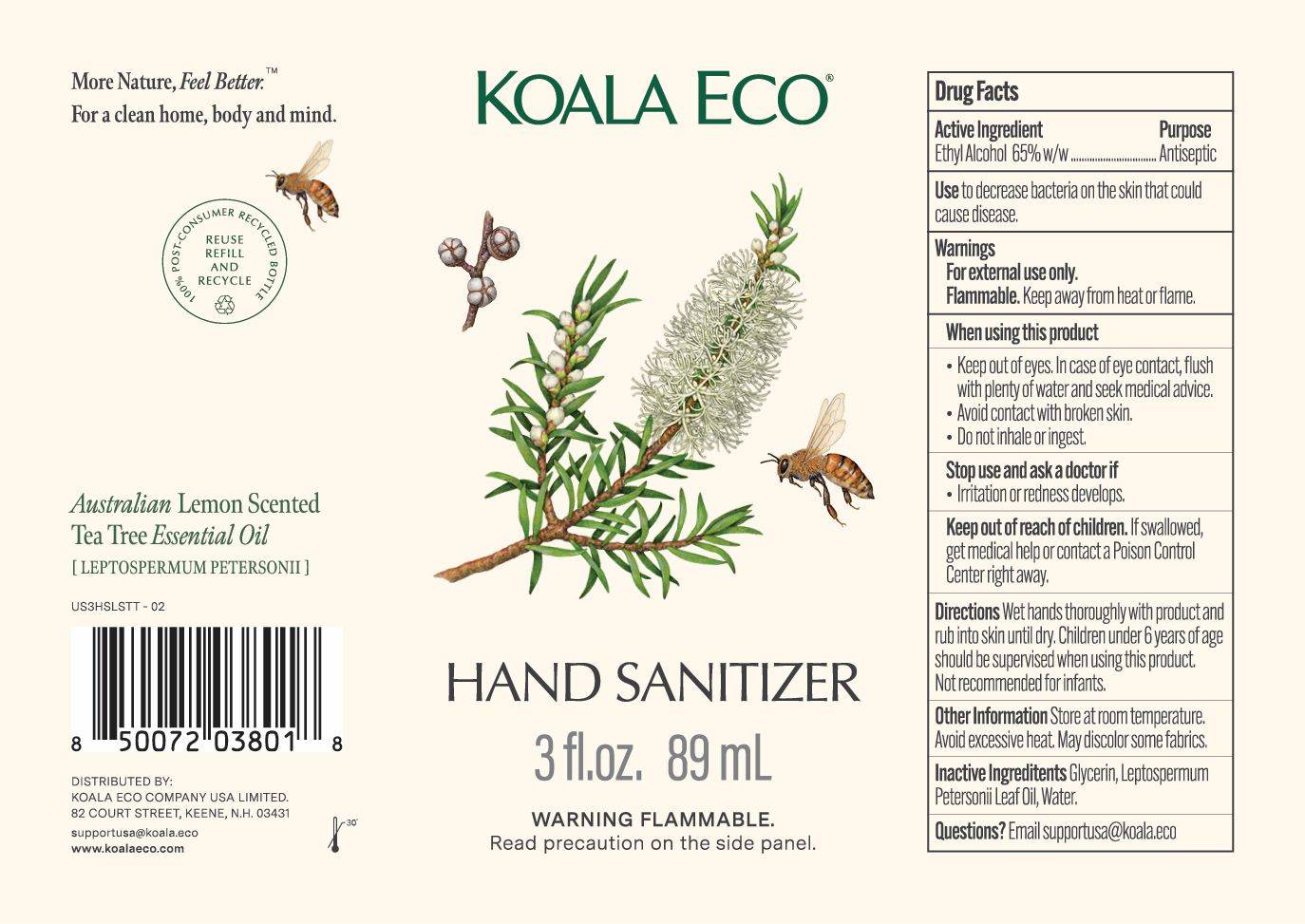 DRUG LABEL: Koala Eco Hand Sanitizer
NDC: 87177-001 | Form: LIQUID
Manufacturer: Koala Eco Company USA Ltd
Category: otc | Type: HUMAN OTC DRUG LABEL
Date: 20251023

ACTIVE INGREDIENTS: ALCOHOL 650 mg/1 mL
INACTIVE INGREDIENTS: WATER; LEPTOSPERMUM PETERSONII LEAF OIL; GLYCERIN

Koala Eco Hand Sanitizer

Active Ingredient

Ethyl Alcohol 65% w/w

Purpose

Antseptic

Use

To decrease bacteria on the skin that could cause disease

Warnings

For external use only

Flammable. Keep away from heat or flame.

When using this product

- Keep out of eyes. In case of eye contact, flush with plenty of water and seek medical advice.
- Avoid contact with broken skin
- Do not inhale or ingest

Stop use

Stop use and ask a doctor if irritation or redness develops

Keep out of reach of children

If swallowed, get medical help or contact a Poison Control Center right away.

Directions

Wet hands thoroughly with product and rub into skin until dry. Children under 6 years of age should be supervised when usiing this product. Not recommended for infants.

Other Information

Store at room temperature. Avoid excessive heat. May discolor some fabrics.

Inactive Ingredients

Glycerin

Leptospermum Petersonii Leaf Oil

Water

Questions?

Email supportusa@koalaeco